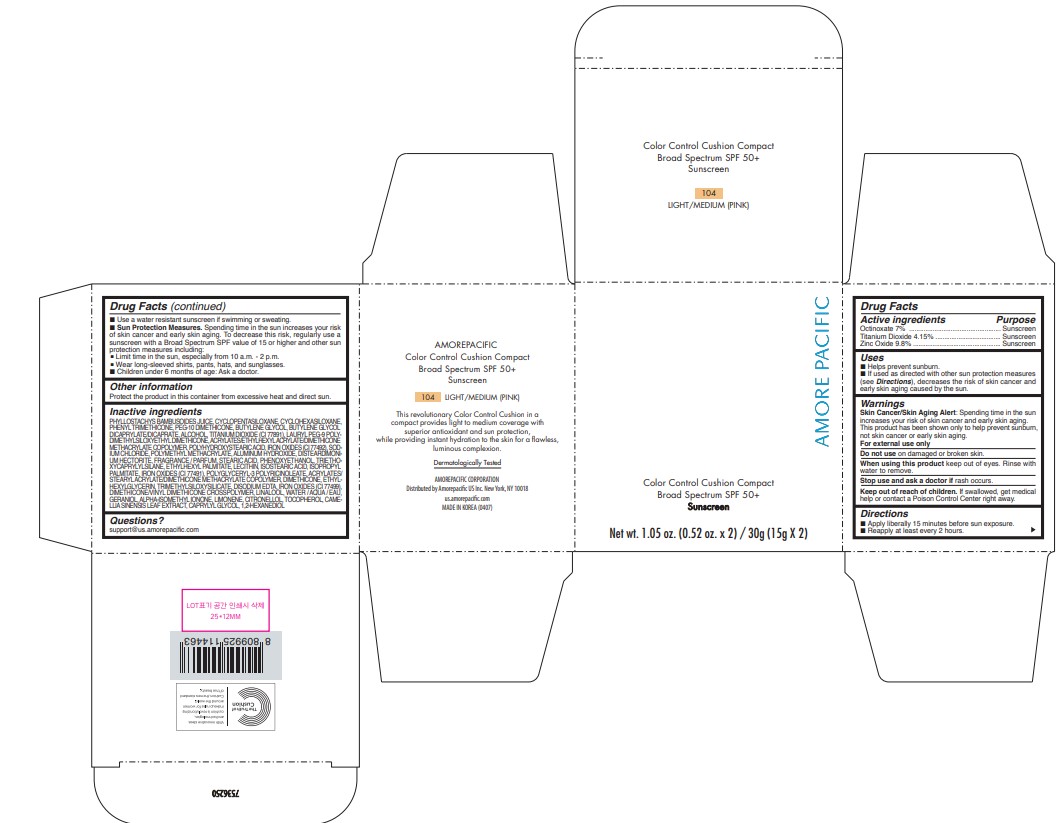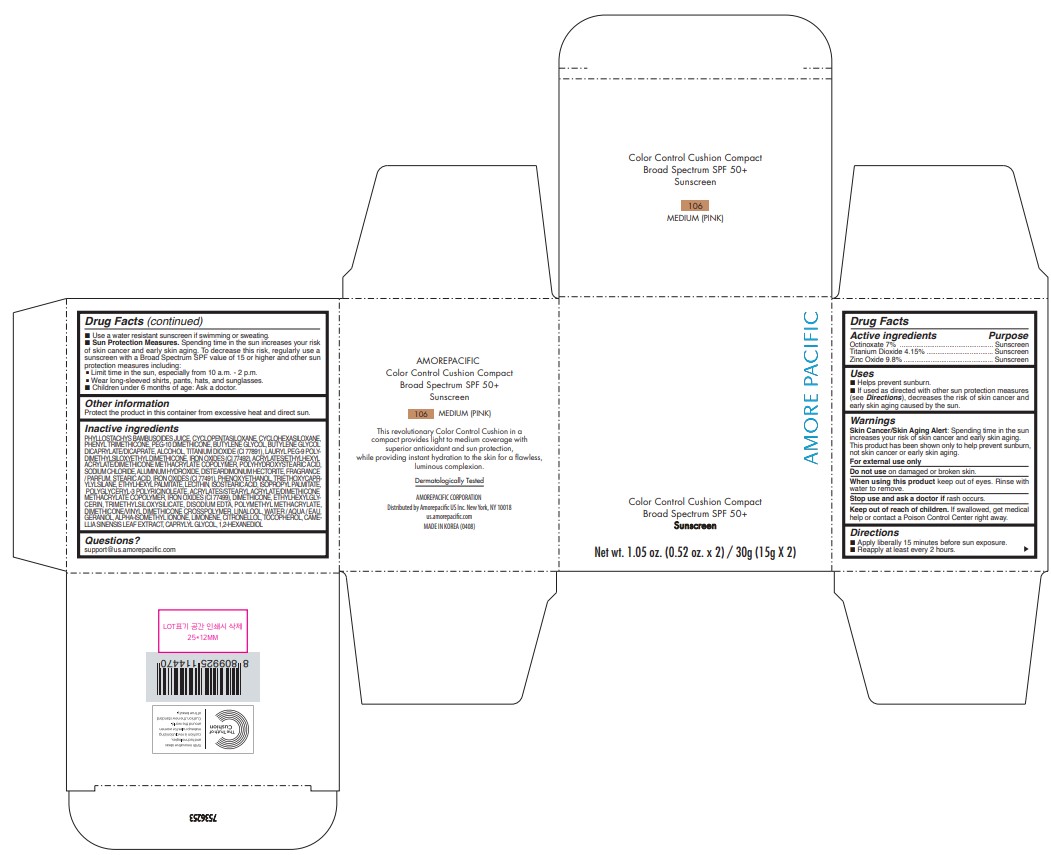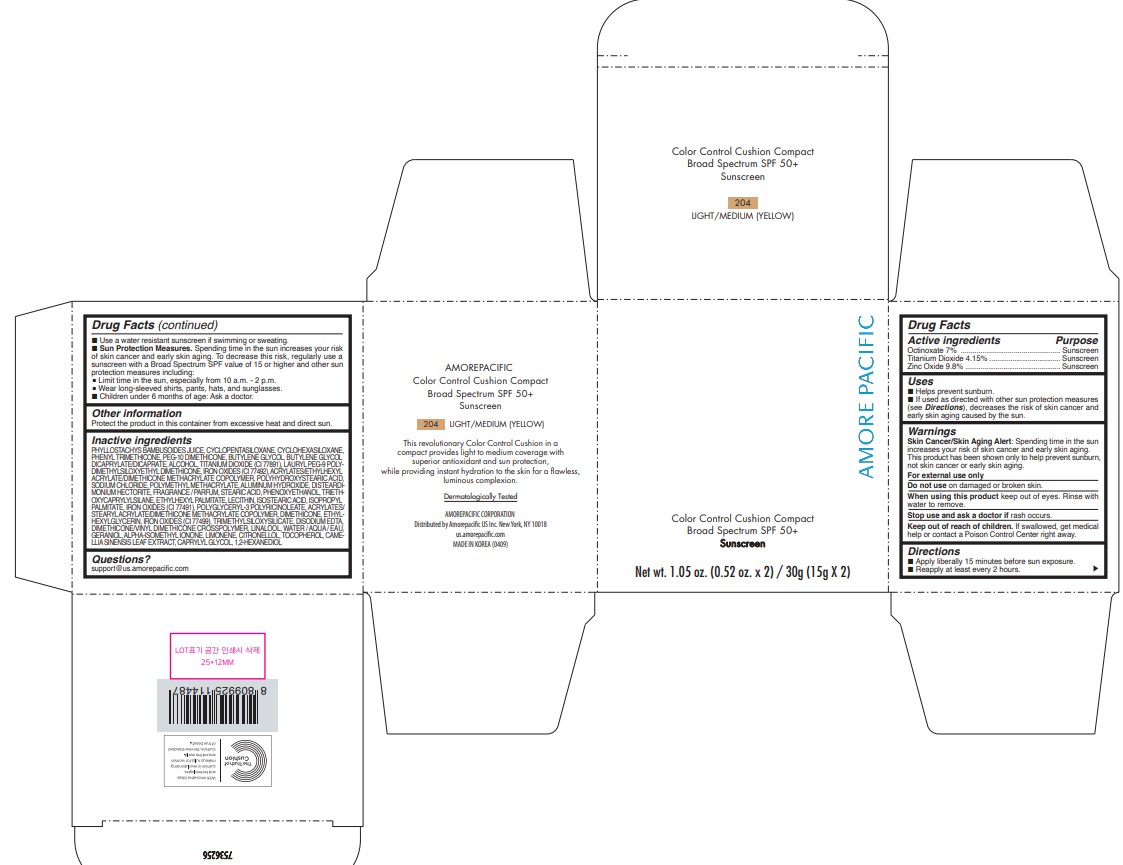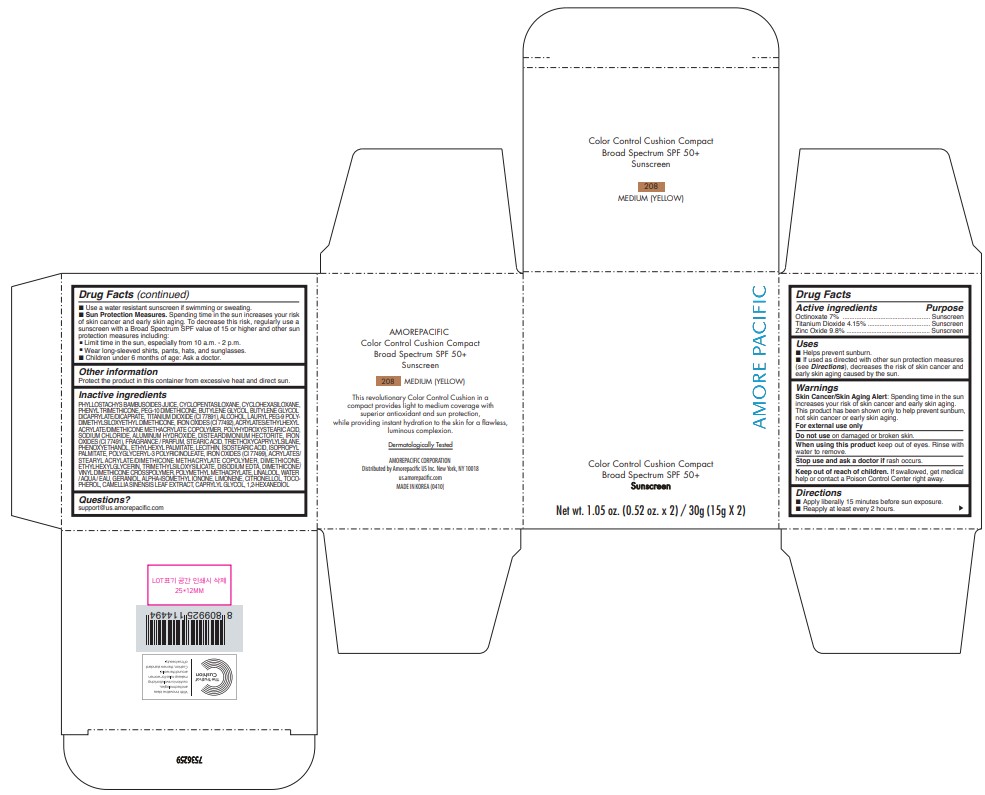 DRUG LABEL: AMOREPACIFIC
NDC: 43419-512 | Form: LOTION
Manufacturer: AMOREPACIFIC CORPORATION
Category: otc | Type: HUMAN OTC DRUG LABEL
Date: 20241008

ACTIVE INGREDIENTS: OCTINOXATE 1.05 g/15 g; TITANIUM DIOXIDE 0.6225 g/15 g; ZINC OXIDE 1.47 g/15 g
INACTIVE INGREDIENTS: TOCOPHEROL; POLYGLYCERYL-3 RICINOLEATE; TRIMETHYLSILOXYSILICATE (M/Q 0.66); DIMETHICONE/VINYL DIMETHICONE CROSSPOLYMER (SOFT PARTICLE); PHYLLOSTACHYS RETICULATA RESIN; CYCLOMETHICONE 5; CYCLOMETHICONE 6; PEG-10 DIMETHICONE (600 CST); PHENYL TRIMETHICONE; BUTYLENE GLYCOL; BUTYLENE GLYCOL DICAPRYLATE/DICAPRATE; ALCOHOL; SODIUM CHLORIDE; ALUMINUM HYDROXIDE; LAURYL PEG-9 POLYDIMETHYLSILOXYETHYL DIMETHICONE; STEARIC ACID; TRIETHOXYCAPRYLYLSILANE; ETHYLHEXYL PALMITATE; EGG PHOSPHOLIPIDS; ISOSTEARIC ACID; ISOPROPYL PALMITATE; PHENOXYETHANOL; DIMETHICONE; EDETATE DISODIUM; ETHYLHEXYLGLYCERIN; WATER; GREEN TEA LEAF; CAPRYLYL GLYCOL; 1,2-HEXANEDIOL; FERRIC OXIDE YELLOW; FERRIC OXIDE RED; FERROSOFERRIC OXIDE; POLYHYDROXYSTEARIC ACID (2300 MW); POLY(METHYL METHACRYLATE; 450000 MW); EDETATE DISODIUM ANHYDROUS

AMOREPACIFIC COLOR CONTROL CUSHION COMPACT

Drug Facts

ACTIVE INGREDIENTS

ETHYLHEXYL METHOXYCINNAMATE 7%
TITANIUM DIOXIDE 4.15%
ZINC OXIDE 9.8%

PURPOSE

Sunscreen

USES

- Helps prevent sunburn.
- If used as directed with other sun protection measures (see Directions), decreases the risk of skin cancer and early skin aging caused by the sun.

WARNINGS

- For external use only.

- Do not use on damaged or broken skin.

- When using this product keep out of eyes. Rinse with water to remove.

- Stop use and ask a doctor if rash occurs.

- Keep out of reach of children. If product is swallowed, get medical help or contact a Poison Control Center right away.

DIRECTIONS

- Apply liberally 15 minutes before sun exposure.
- Reapply at least every 2 hours.
- Use a water-resistant sunscreen if swimming or sweating.
- Sun Protection Measures. Spending time in the sun increases your risk of skin cancer and early skin aging. To decrease this risk, regularly use a sunscreen with a Broad Spectrum SPF value of 15 or higher and other sun protection measures including:
  - Limit time in the sun, especially from 10 a.m. - 2 p.m.
  - Wear long-sleeved shirts, pants, hats, and sunglasses.
- Children under 6 months of age: Ask a doctor.

INACTIVE INGREDIENTS

PHYLLOSTACHYS BAMBUSOIDES JUICE, CYCLOPENTASILOXANE, CYCLOHEXASILOXANE, PHENYL TRIMETHICONE, PEG-10 DIMETHICONE, BUTYLENE GLYCOL, BUTYLENE GLYCOL DICAPRYLATE/DICAPRATE, ALCOHOL, TITANIUM DIOXIDE (CI 77891), LAURYL PEG-9 POLY[1]DIMETHYLSILOXYETHYL DIMETHICONE, ACRYLATES/ETHYLHEXYL ACRYLATE/DIMETHICONE METHACRYLATE COPOLYMER, POLYHYDROXYSTEARIC ACID, IRON OXIDES (CI 77492), SOD[1]IUM CHLORIDE, POLYMETHYL METHACRYLATE, ALUMINUM HYDROXIDE, DISTEARDIMONI[1]UM HECTORITE, FRAGRANCE / PARFUM, STEARIC ACID, PHENOXYETHANOL, TRIETHO[1]XYCAPRYLYLSILANE, ETHYLHEXYL PALMITATE, LECITHIN, ISOSTEARIC ACID, ISOPROPYL PALMITATE, IRON OXIDES (CI 77491), POLYGLYCERYL-3 POLYRICINOLEATE, ACRYLATES/ STEARYL ACRYLATE/DIMETHICONE METHACRYLATE COPOLYMER, DIMETHICONE, ETHYL[1]HEXYLGLYCERIN, TRIMETHYLSILOXYSILICATE, DISODIUM EDTA, IRON OXIDES (CI 77499), DIMETHICONE/VINYL DIMETHICONE CROSSPOLYMER, LINALOOL, WATER / AQUA / EAU, GERANIOL, ALPHA-ISOMETHYL IONONE, LIMONENE, CITRONELLOL, TOCOPHEROL, CAME[1]LLIA SINENSIS LEAF EXTRACT, CAPRYLYL GLYCOL, 1,2-HEXANEDIOL

OTHER INFORMATION

Protect the product in this container from excessive heat and direct sun

Questions?

support@us.amorepacific.com

PRINCIPAL DISPLAY PANEL - 30 g Container Carton - 104 LIGHT/MEDIUM (PINK)

Amore Pacific

Color Control Cushion Compact

Broad Spectrum SPF 50+

Sunscreen

Net wt. 1.05 oz. (0.52 oz. x 2) / 30g (15g X 2)

PRINCIPAL DISPLAY PANEL - 30 g Container Carton - 106 MEDIUM (PINK)

AMORE PACIFIC

COLOR CONTROL CUSHION COMPACT
Broad Spectrum SPF 50+
Sunscreen

Net wt. 1.05 oz. (0.52 oz. x 2) / 30g (15g X 2)

PRINCIPAL DISPLAY PANEL - 30 g Container Carton - 204 LIGHT/MEDIUM (YELLOW)

AMORE PACIFIC

COLOR CONTROL CUSHION COMPACT
Broad Spectrum SPF 50+
Sunscreen

Net wt. 1.05 oz. (0.52 oz. x 2) / 30g (15g X 2)

PRINCIPAL DISPLAY PANEL - 30 g Container Carton - 208 MEDIUM (YELLOW)

AMOREPACIFIC

COLOR CONTROL CUSHION COMPACT
Broad Spectrum SPF 50+
Sunscreen

Net wt. 1.05 oz. (0.52 oz. x 2) / 30g (15g X 2)